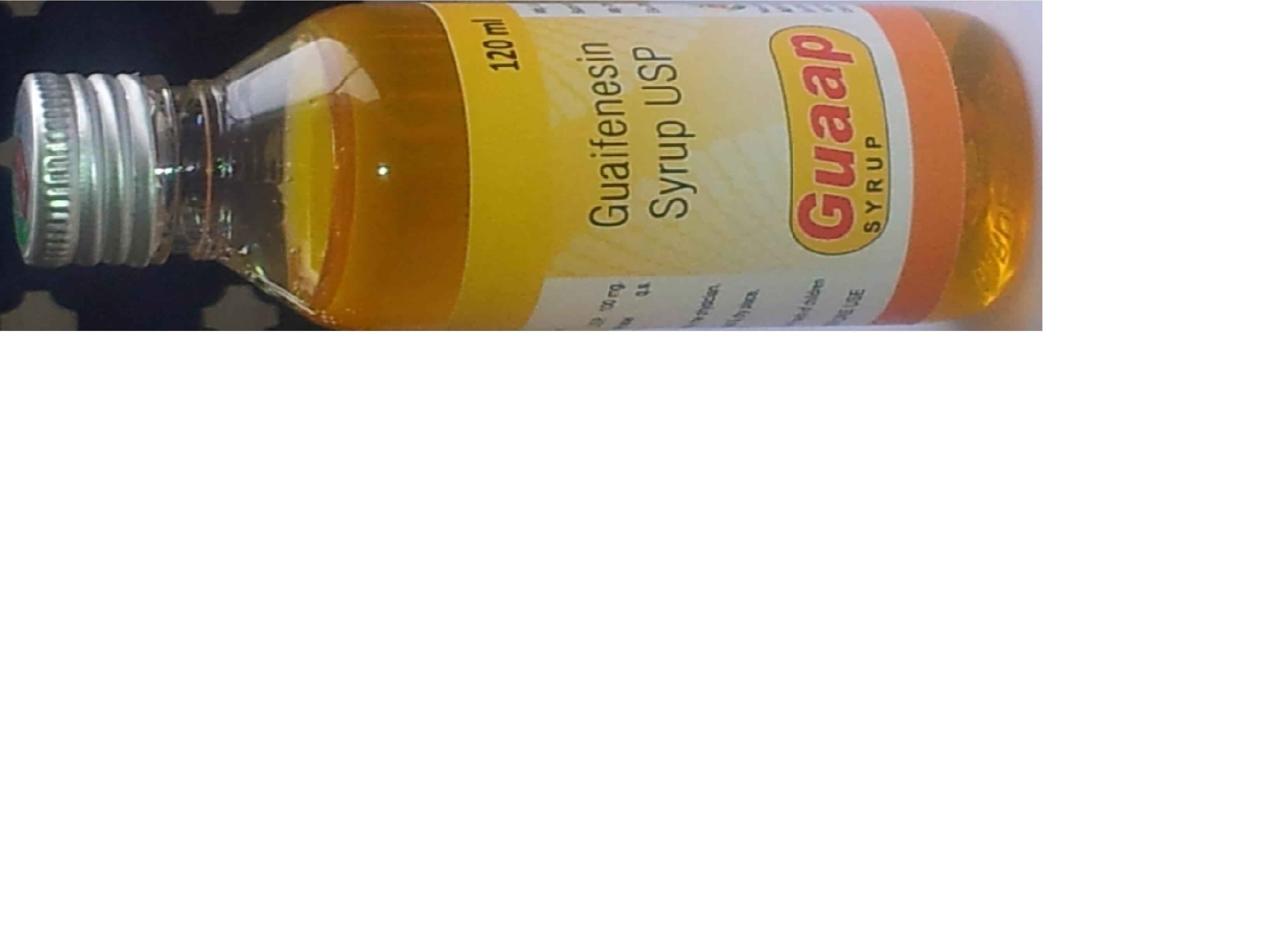 DRUG LABEL: GUAAP
NDC: 46084-051 | Form: LIQUID
Manufacturer: A P J Laboratories Limited
Category: otc | Type: HUMAN OTC DRUG LABEL
Date: 20130228

ACTIVE INGREDIENTS: GUAIFENESIN 100 mg/5 mL
INACTIVE INGREDIENTS: MENTHOL 10 ug/5 mL; SUCROSE 200 mg/5 mL; SORBITOL 50 mg/5 mL; SODIUM BENZOATE 1 mg/5 mL; BRONOPOL 0.5 mg/5 mL; EDETIC ACID     0.5 mg/5 mL; ASPARTAME 1 mg/5 mL; XANTHAN GUM 0.5 mg/5 mL

purpose

Expectorant

keep out of reach of children

In case of overdose, get medical help or contact a Poison Control Center right away.

uses

helps loosen phlegm (mucus) and thin bronchial secretions to make coughs more productive.

warning

Ask a doctor before use if you have
•cough that occurs with too much phlegm (mucus)
•cough that lasts or is chronic such as occurs with smoking, asthma, chronic bronchitis, or emphysema
Stop use and ask a doctor if
cough lasts for more than 7 days, comes back, or occurs with fever, rash, or persistent headache. A persistent cough may be a sign of a serious condition.

direction

•do not take more than 6 doses in any 24-hour period

•this adult product is not intended for use in children under 12 years of age
age dose

adults and children 12 years and over: 2-4 teaspoons every 4 hours

children under 12 years: do not use

inactive ingredient

ASPARTAME

INACTIVE INGREDIENT

BRONOPOL

INACTIVE INGREDIENT

EDETIC ACID

INACTIVE INGREDIENT

MENTHOL

INACTIVE INGREDIENT

SUCROSE

INACTIVE INGREDIENT

SODIUM BENZOATE

INACTIVE INGREDIENT

SORBITOL

INACTIVE INGREDIENT

XANTHAN GUM

ACTIVE INGREDIENT

GUAIFENESIN